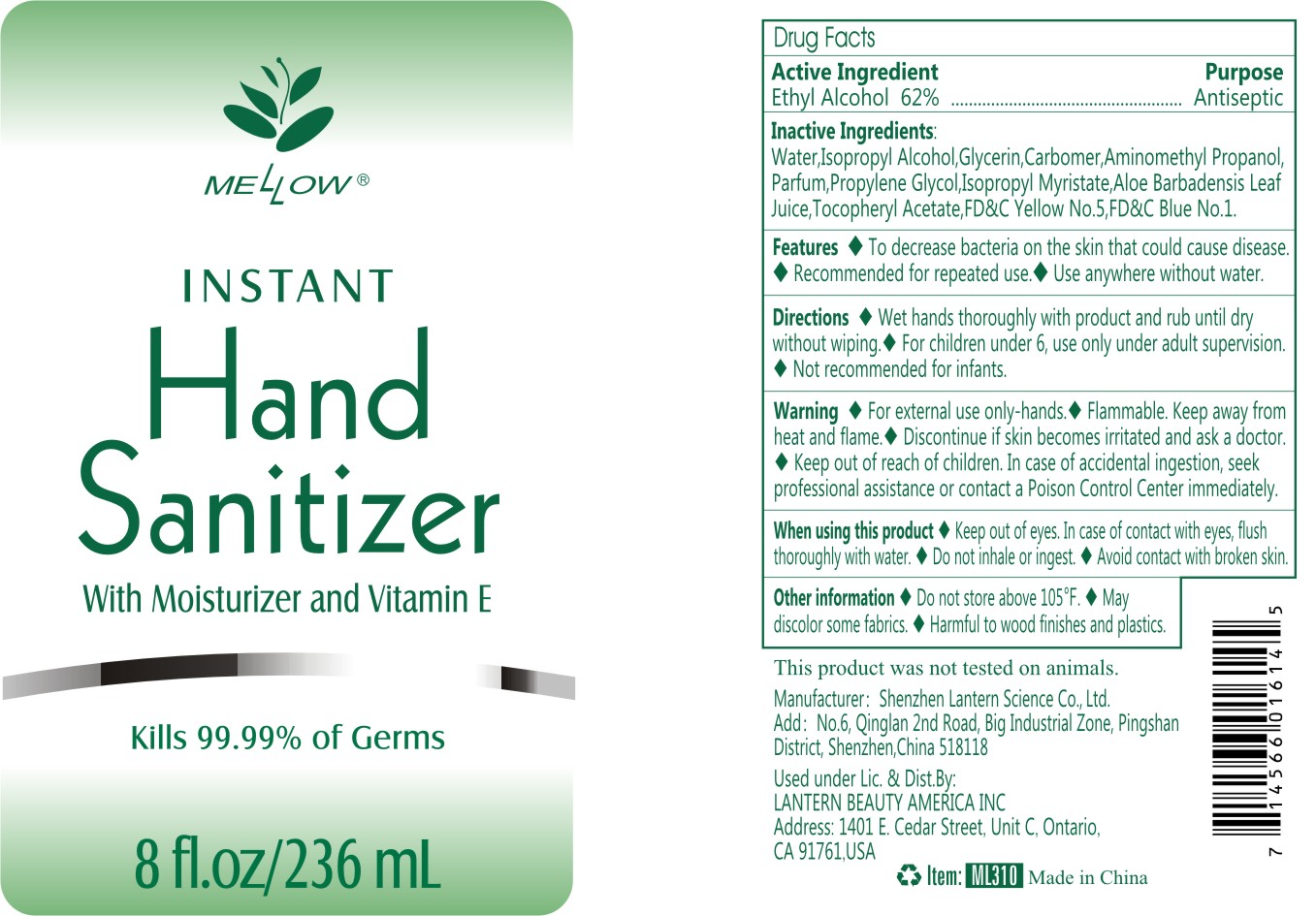 DRUG LABEL: Mellow hand sanitizer236ml ML310
NDC: 54860-396 | Form: LIQUID
Manufacturer: Shenzhen Lantern Science Co.,Ltd
Category: otc | Type: HUMAN OTC DRUG LABEL
Date: 20220425

ACTIVE INGREDIENTS: ALCOHOL 62 mL/100 mL
INACTIVE INGREDIENTS: ALOE VERA LEAF 0.1 mL/100 mL; ALOE 0.2 mL/100 mL; ISOPROPYL MYRISTATE 0.001 mL/100 mL; CARBOMER 940 0.4 mL/100 mL; WATER 36.057972 mL/100 mL; ISOPROPYL ALCOHOL 0.5 mL/100 mL; FD&C YELLOW NO. 5 0.00002 mL/100 mL; AMINOMETHYLPROPANOL 0.14 mL/100 mL; FD&C BLUE NO. 1 0.000008 mL/100 mL; GLYCERIN 0.5 mL/100 mL; PROPYLENE GLYCOL 0.1 mL/100 mL; .ALPHA.-TOCOPHEROL ACETATE 0.001 mL/100 mL

Mellow hand sanitizer 236ml ML310

Active Ingredient

Active Ingredients Purpose

Ethyl Alcohol 62% Antiseptic

Feature

To decrease bacteria on the skin that could cause disease.

Recommended for repeated use.

Use anywhere without water.

DOSAGE AND ADMINISTRATION

Recommended for repeated use.

use anywhere without water.

Warning

For external use only:hands,avoid ayes ,in case of eye contact, flush with water.

flammable,keep away from heat and flame.

Discontinue if skin becomes irritated and ask a doctor.

keep out of reach of children,in case of accidenal ingestion.seek professional assistance or contact a poison control center immediately.

WARNINGS AND PRECAUTIONS

For external use only.

Flammable, keep away from heat and flame.

STOP USE

Discontinue if skin becomes irritated and ask a doctor .

Keep out of reach of children. In case of accidental ingestion, seek professional assistance or contact a poson control center immediately.

Inactive ingredients

water，Isopropyl Alcohol，Glycerin，Carbomer，Aminomethyl Propanol，Parfum，Propylene Glycol，ISOPROPYL MYRISTATE，ALOE BARBADENSIS LEAF JUICE，Tocopheryl Acetate，FD&C Yellow No.5(Tartrazine),FD&C Blue No.1.

Directions

wet hands thoroughyly with product and rub until dry without wiping.

For children under 6,use only under adult supervision.

Not recommended for infants.

When using this product

keep out of eyes. In case of contact with eyes, flush thoroughly with water.

Do not inhale or ingest.

Avoid contact with broken skin.

Other information

Do not store above 105F.

May discolor some fabrics.

Harmful to wood finishes and plastics.

OTHER SAFETY INFORMATION

Do not store above100℉（38℃）

May discolor some fabrics.

Harmful to wood finishes and plastics.

When using this product

Keep out of eyes,In case of contact with eyes,flush thoroughly with water.

Do not inhale or ingest.

Avoid contact with broken skin.